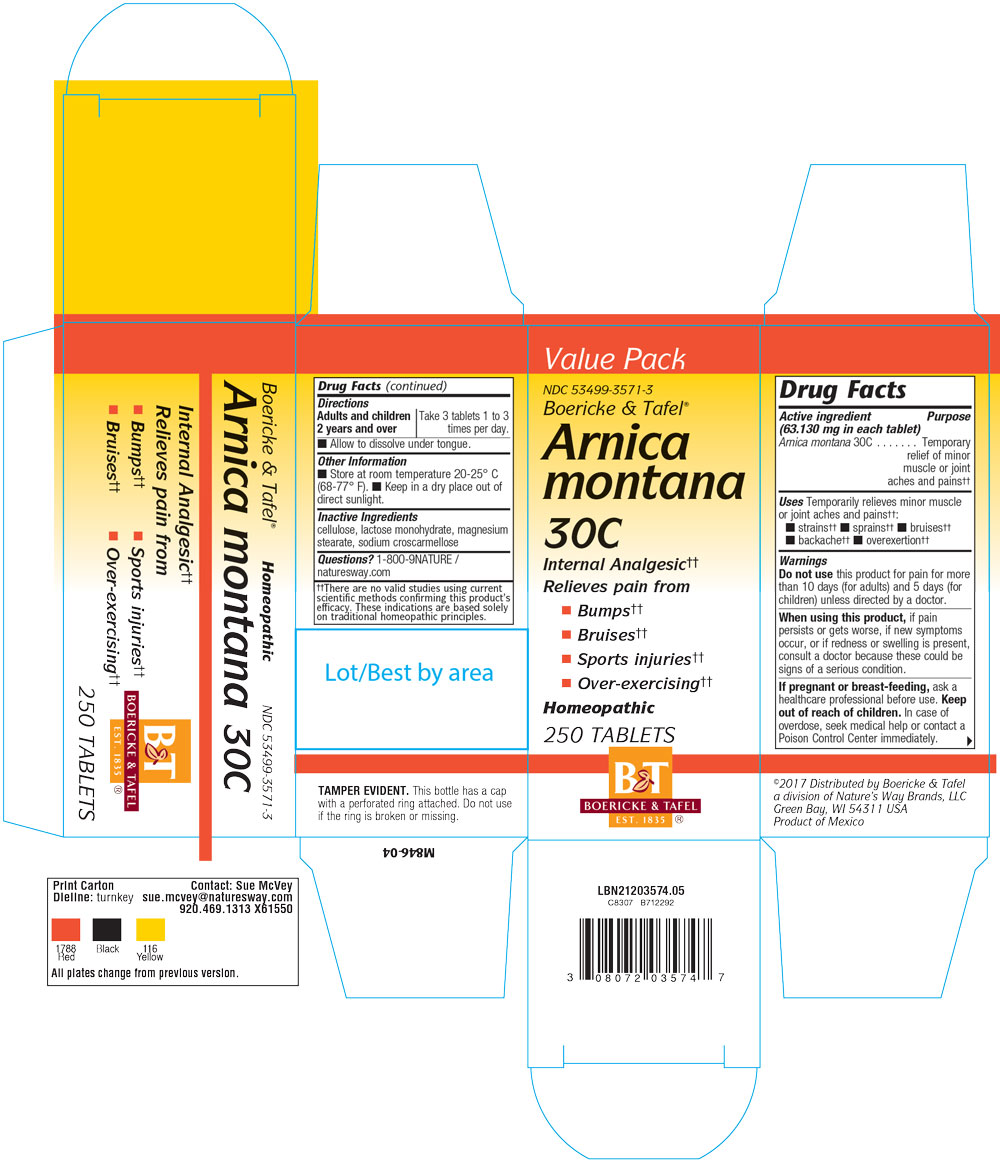 DRUG LABEL: Arnica Montana
NDC: 53499-3571 | Form: TABLET
Manufacturer: Schwabe North America, Inc.
Category: homeopathic | Type: HUMAN OTC DRUG LABEL
Date: 20220520

ACTIVE INGREDIENTS: ARNICA MONTANA 30 [hp_C]/1 1
INACTIVE INGREDIENTS: CELLULOSE, MICROCRYSTALLINE; LACTOSE MONOHYDRATE; MAGNESIUM STEARATE; CROSCARMELLOSE SODIUM

Arnica Montana 30C

Active Ingredient

Arnica Montana 30C

Inactive Ingredients

CELLULOSE

LACTOSE MONOHYDRATE

MAGNESIUM STEARATE

SODIUM CROSCARMELLOSE

Dosage and Administration

Adults or children over 2 years: Take 3 tablets 1 to 3 times per day.

Allow to dissolve under tongue.

Indications and Usage

Temporarily relieves minor muscle or joint aches and pains from strains, sprains, bruises, backache, over extertion.

Purpose

For the temporary relief of minor muscle or joint aches and pains from strains, sprains, bruises, backache and over exertion.

Warnings

Do not use this product for pain for more than 10 days (adult) or 5 days (children) unless directed by a doctor.

When using

When using this product, if pain persists or gets worse, if new symptoms occur, or if redness or swelling is present, consult a doctor because these could be signs of a serous condition.

Pregnancy or Breast Feeding

If you are pregnant or breast-feeding, ask a healthcare professional before use.

Keep out of reach of children

Overdose

In case of overdose, seek medical help or contact a Posion Control Center immediately.